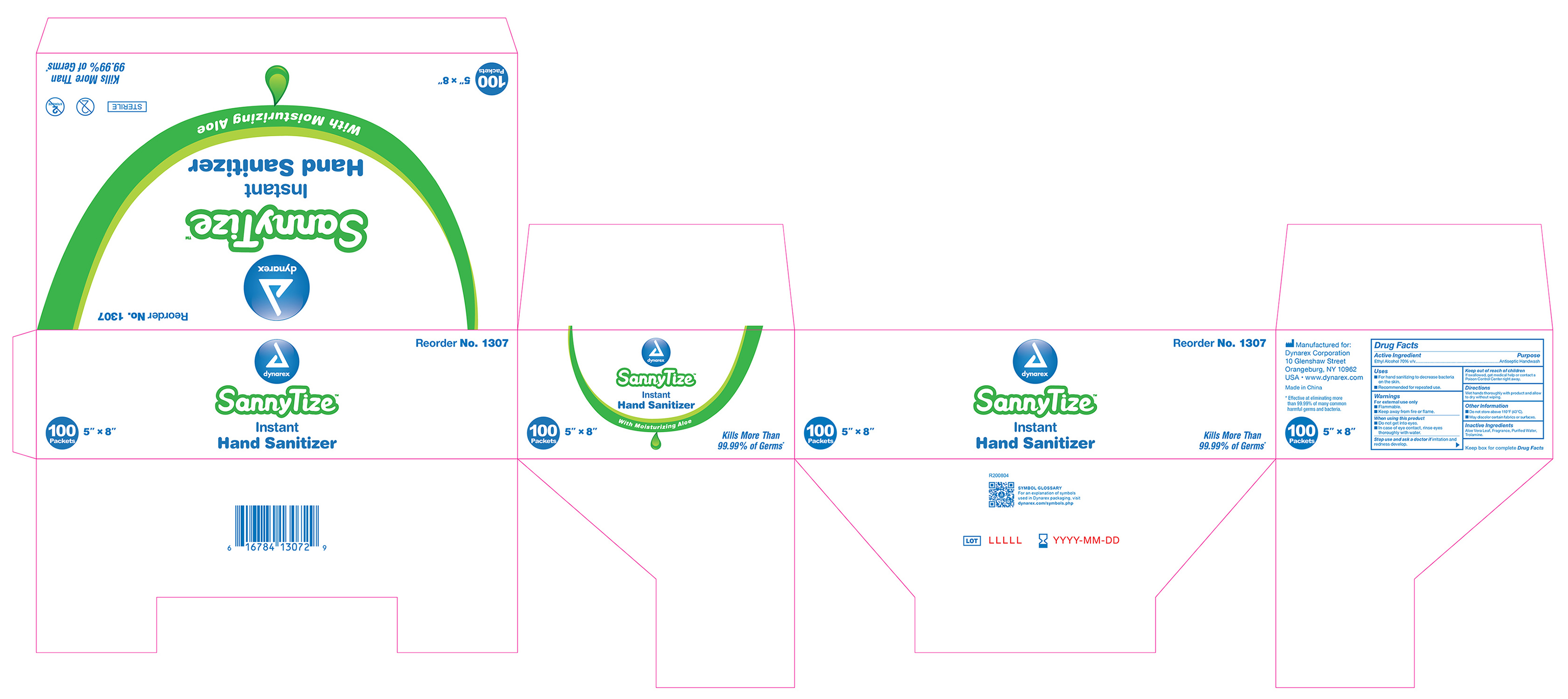 DRUG LABEL: Antimicrobial Sanitizing Hand Wipe
NDC: 67777-330 | Form: SWAB
Manufacturer: Dynarex
Category: otc | Type: HUMAN OTC DRUG LABEL
Date: 20241120

ACTIVE INGREDIENTS: ALCOHOL 70 mL/100 mL
INACTIVE INGREDIENTS: WATER; TROLAMINE; ALOE VERA LEAF

1307 Antimicrobial Sanitizing Hand Wipe, NDC# 67777-330-01

Active Ingredient

Ethyl Alcohol 70% v/v

Purpose

Antiseptic Handwash

Uses

. For hand sanitizing to decrease bacteria on the skin.

. Recommended for repeated use.

Warnings

For External Use Only

. Flammable.

. Keep away from fire or flame.

When using this product

. Do not get into eyes.

. In case of eye contact, rinse eyes thoroughly with water.

Stop use and ask a doctor if

irritation and redness develop.

Keep out of reach of children

If swallowed, get medical help or contact a Poison Control Center right away.

Directions

Wet hands thoroughly with product and allow to dry without wiping.

Other Information

. Do not store above 110°F (43ºC).

. May discolor certain fabrics or surfaces.

Inactive Ingredients

Aloe Vera Leaf, Fragrance, Purified Water, Trolamine.

1307 Antimicrobial Sanitizing Hand Wipe Label